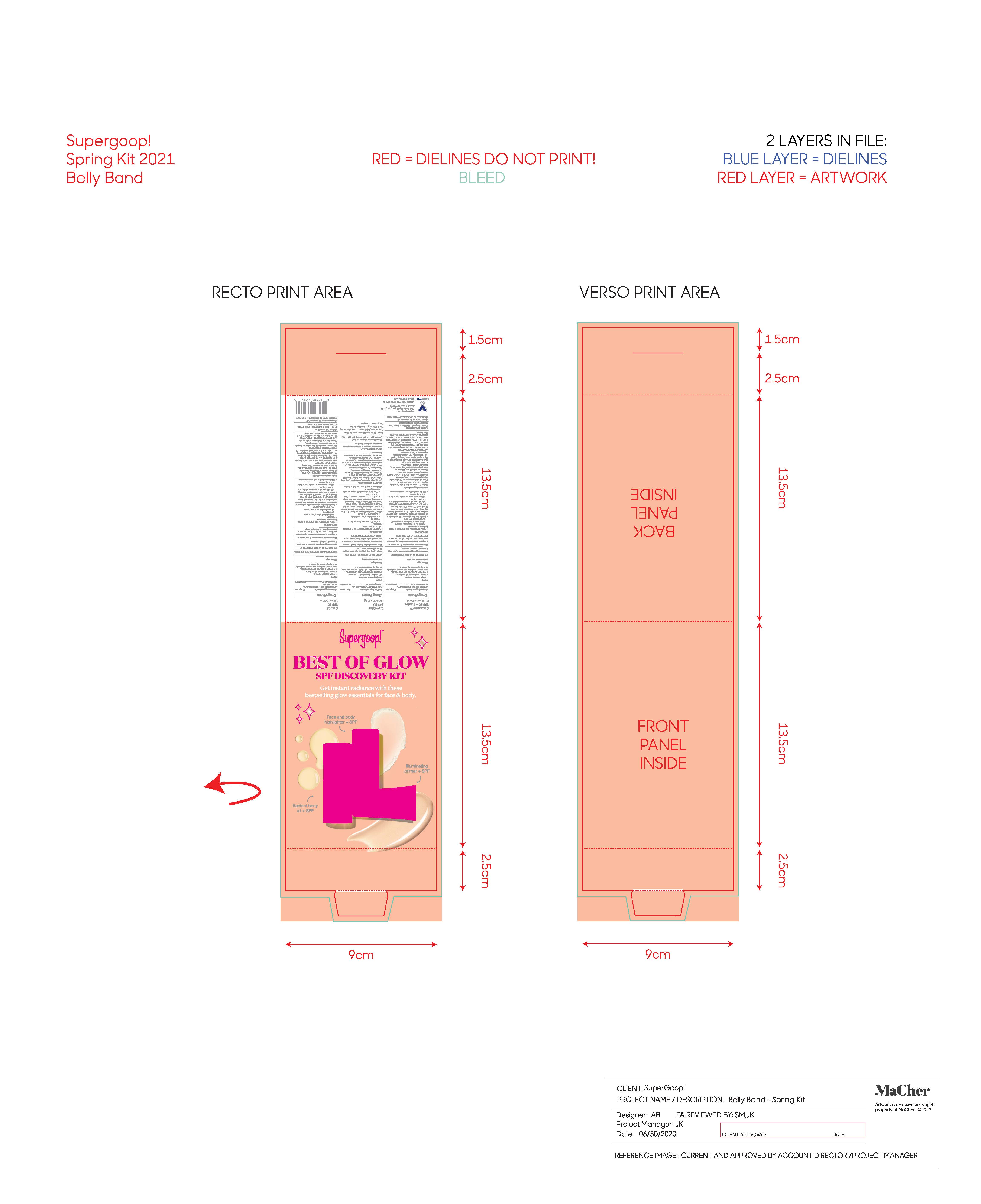 DRUG LABEL: Best of Glow SPF Discovery Kit
NDC: 75936-418 | Form: KIT | Route: TOPICAL
Manufacturer: Supergoop, LLC
Category: otc | Type: HUMAN OTC DRUG LABEL
Date: 20220929

ACTIVE INGREDIENTS: OCTOCRYLENE 10 g/100 mL; AVOBENZONE 3 g/100 g; OCTISALATE 5 g/100 g; OCTOCRYLENE 10 g/100 g; HOMOSALATE 10 g/100 mL; AVOBENZONE 3 g/100 mL; OCTISALATE 5 g/100 mL; OCTOCRYLENE 10 g/100 mL
INACTIVE INGREDIENTS: AVOBENZONE 3 g/100 mL; OCTISALATE 5 g/100 mL; DIETHYLHEXYL SYRINGYLIDENEMALONATE; MAURITIA FLEXUOSA FRUIT OIL; TAMANU OIL; SUNFLOWER OIL; DIBUTYL LAUROYL GLUTAMIDE; ISOHEXADECANE; TOCOPHEROL; ISODODECANE; MEADOWFOAM SEED OIL FATTY ACIDS; DICAPRYLYL CARBONATE; ALKYL (C12-15) BENZOATE; OCTYLDODECANOL; CALENDULA OFFICINALIS FLOWER; MEDIUM-CHAIN TRIGLYCERIDES; POLYESTER-8 (1400 MW, CYANODIPHENYLPROPENOYL CAPPED); DIBUTYL ETHYLHEXANOYL GLUTAMIDE; PENTACLETHRA MACROLOBA SEED OIL; DIETHYLHEXYL SYRINGYLIDENEMALONATE; PENTAERYTHRITOL TETRAKIS(3-(3,5-DI-TERT-BUTYL-4-HYDROXYPHENYL)PROPIONATE); CUCUMBER; SHEA BUTTER; LAURYL LACTATE; SUNFLOWER OIL; ARGAN OIL; GRAPE SEED OIL; ISODECYL NEOPENTANOATE; ALCOHOL; DENATONIUM BENZOATE; CITRIC ACID MONOHYDRATE; COCONUT OIL; POLYESTER-8 (1400 MW, CYANODIPHENYLPROPENOYL CAPPED); ALKYL (C12-15) BENZOATE; SOYBEAN OIL; ALARIA ESCULENTA; MEADOWFOAM SEED OIL; TERT-BUTYL ALCOHOL; DIISOPROPYL SEBACATE; TOCOPHEROL; OCTYLDODECANOL; POLYAMIDE-3 (12000 MW); MEDIUM-CHAIN TRIGLYCERIDES

DTC Glow Kit

Glowscreen Active Ingredient

Avobenzone 3% Sunscreen

Octisalate 5% Sunscreen

Octocrylene 10% Sunscreen

Glow Oil Active Ingredient

Avobenzone 3% Sunscreen

Homosalate 10% Sunscreen

Octisalate 5% Sunscreen

Octocrylene 10% Sunscreen

Glow Stick Active Ingredient

Avobenzone 3% Sunscreen

Octisalate 5% Sunscreen

Octocrylene 10% Sunscreen

Uses

Helps prevent Sunburn

If used as directed with other sun protection measures (see Directions), decreases the risk of Skin cancer and early skin aging caused by the sun

Keep out of reach of children. If product is swallowed, get medical help or contact Poison Control Center right away.

Stop use and ask a doctor if rash occurs.

WARNINGS

For External use only

Do not use on damaged or broken skin

When using this product, Keep out of eyes. Rinse with water to remove

Glowscreen SPF 40

• apply generously and evenly 15 minutes before sun exposure
• reapply at least every 2 hours
• use a water resistant sunscreen if swimming or sweating

Sun Protection Measures: Spending time in the sun increases your risk of skin cancer and early skin aging. To decrease this risk, regularly use a sunscreen with a Broad Spectrum SPF value of 15 or higher and other sun protection measures including: • Limit time in the sun, especially from 10 a.m. – 2 p.m.• Wear long-sleeved shirts, pants, hats, and sunglasses • Children under 6 months: Ask a doctor

Glow Oil SPF 50

• apply generously and evenly 15 minutes before sun exposure
• reapply:
• after 80 minutes of swimming or sweating
• immediately after towel drying
• at least every 2 hours

Sun Protection Measures: Spending time in the sun increases your risk of skin cancer and early skin aging. To decrease this risk, regularly use a sunscreen with a Broad Spectrum SPF value of 15 or higher and other sun protection measures including: • Limit time in the sun, especially from 10 a.m. – 2 p.m.• Wear long-sleeved shirts, pants, hats, and sunglasses • Children under 6 months: Ask a doctor

Glow Stick SPF 50

• apply generously and evenly 15 minutes before sun exposure
• reapply at least every 2 hours
• use a water resistant sunscreen if swimming or sweating

Sun Protection Measures: Spending time in the sun increases your risk of skin cancer and early skin aging. To decrease this risk, regularly use a sunscreen with a Broad Spectrum SPF value of 15 or higher and other sun protection measures including: • Limit time in the sun, especially from 10 a.m. – 2 p.m.• Wear long-sleeved shirts, pants, hats, and sunglasses • Children under 6 months: Ask a doctor

Glowscreen SPF 40

Inactive Ingredients: Water, Propanediol, Butyloctyl Salicylate, Glycerin, C12-15 Alkyl Benzoate, Polymethylsilsesquioxane, Niacinamide, Glyceryl Stearate Citrate, Bismuth Oxychloride, Mica, Titanium Dioxide, Lauryl Lactate, Isododecane, Isodecyl Neopentanoate, Glyceryl Stearate, Diisopropyl Sebacate, Cetyl Phosphate, Caprylic/Capric Triglyceride, Coco-Caprylate, Ethylhexyl Hydroxystearate, Butylene Glycol, Arginine, Hydroxyacetophenone, Caprylyl Glycol, 1,2-Hexanediol, Iron Oxides, Sodium Hyaluronate, Chlorphenesin, Acrylates/C10-30 Alkyl Acrylate Crosspolymer, Trisodium Ethylenediamine Disuccinate, Phospholipids, Limonium Gerberi Extract, Leuconostoc/Radish Root Ferment Filtrate, Theobroma Cacao (Cocoa) Seed Extract, Pantothenic Acid, Tocopherol, Helianthus Annuus (Sunflower) Seed Oil, Ferulic Acid

Glow Stick SPF 50

Inactive Ingredients: C12-15 Alkyl Benzoate , Calendula Officinalis Extract, Calophyllum Inophyllum Seed Oil, Caprylic/Capric Triglyceride, Dibutyl Ethylhexanol Glutamide, Dibutyl Lauroyl Glutamide, Dicaprylyl Carbonate, Diethylhexyl Syringylidenemalonate, Helianthus Annuus (Sunflower) Seed Oil, Isododecane, Isohexadecane, Limnanthes Alba (Meadowfoam) Seed Oil, Mauritia Flexuosa Fruit Oil, Octyldodecanol, Pentaclethra Macroloba Oil, Polyester-8, Tocopherol

Glow Oil SPF 50

Inactive Ingredients: Caprylic/Capric Triglyceride, Alcohol, Octyldodecanol, C12-15 Alkyl Benzoate, Polyester-8, Polyamide-3, Lauryl Lactate, Isodecyl Neopentanoate, Diisopropyl Sebacate, Diethylhexyl Syringylidenemalonate, Tocopherol, Glycine Soja (Soybean) Oil, Vitis Vinifera (Grape) Seed Oil, Raphanus Sativus (Radish) Seed Oil, Limnanthes Alba (Meadowfoam) Seed Oil, Helianthus Annuus (Sunflower) Seed Oil, Cocos Nucifera (Coconut) Oil, Butyrospermum Parkii (Shea) Butter, Argania Spinosa Kernel Oil, Pentaerythrityl Tetra-di-t-butyl Hydroxyhydrocinnamate, Alaria Esculenta Extract, t-Butyl Alcohol, Cucumis Sativus (Cucumber) Fruit Extract, Denatonium Benzoate, Citric Acid

Best of Glow SPF Discovery Kit Belly Band

Supergoop!

Best of Glow

SPF Discovery Kit

Glowscreen SPF 40 - Sunrise

0.5 fl. oz. / 15 mL

Glow Stick SPF 50

0.70 oz. / 20 g

Glow Oil SPF 50

1 fl. oz. / 30 mL